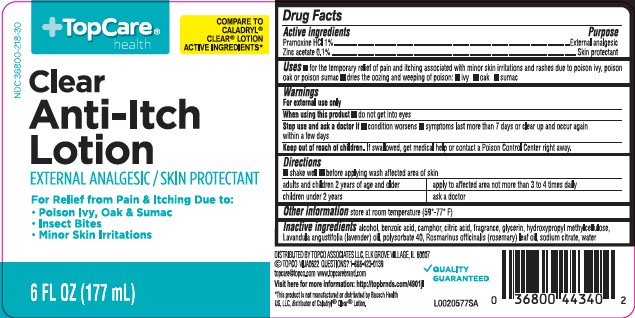 DRUG LABEL: Clear Anti Itch
NDC: 36800-218 | Form: LOTION
Manufacturer: Topco Associates LLC
Category: otc | Type: HUMAN OTC DRUG LABEL
Date: 20260213

ACTIVE INGREDIENTS: PRAMOXINE HYDROCHLORIDE 10 mg/1 mL; ZINC ACETATE 1 mg/1 mL
INACTIVE INGREDIENTS: ALCOHOL; BENZOIC ACID; CAMPHOR (NATURAL); CITRIC ACID MONOHYDRATE; GLYCERIN; HYPROMELLOSE, UNSPECIFIED; LAVENDER OIL; POLYSORBATE 40; ROSEMARY OIL; SODIUM CITRATE; WATER

Top Care 218.002/218AF
Clear Anti-Itch Lotion

Active Ingredients

Pramoxine HCl 1%

Zinc acetate 0.1%

Purpose

External analgesic

Skin protectant

Uses

- for the temporary relief of pain and itching associated with minor skin irritations and rashes due to poison ivy, poison oak or poison sumac
- dries the oozing and weeping of poison:
- ivy
- oak
- sumac

Warnings

For external use only

When using this product

do not get into eyes

Stop use and ask a doctor if

- condition worsens
- symptoms last more than 7 days or clear up and occur again within a few days

Keep out of reach of children.

If swallowed, get medical help or contact a Poison Control Center right away.

Directions

- shake well
- before applying was affected are of skin

adults and children 2 years of age and older - apply to affected area not more than 3 to 4 times daily

children under 2 years of age - ask a doctor

Other information

store at room temperature (59°-77°F)

Inactive ingredients

alcohol, benzoic acid, camphor, citric acid, fragrance, glycerin, hydroxypropyl methylcellulose, Lavandula angustifolia (lavender) oil, polysorbate 40, Rosmarinus officinalis (rosemary) leaf oil, sodium citrate, water

ADVERSE REACTION

DISTRIBUTED BY TOPCO ASSOCIATES LLC, ELK GROVE VILLAGE, IL 60007

©TOPCO VIJA0622 Questions? 1-888-423-0139

topcare@topco.com www.topcarebrand.com

Visit here for more information: http:/topbrnds.com/4901jl

Quality Guaranteed

Disclaimer

*This product is not manufactured of distributed by Bausch Health US, LLC, distributer of Caladryl®Clear®Lotion.

principal display panel

TopCare®health

NDC 36800-218-30

COMPARE TO CALADRYL®CLEAR®LOTION ACTIVE INGREDIENTS*

Clear Anti-Itch Lotion

EXTERNAL ANALGESIC / SKIN PROTECTANT

For Relief of Pain and Itching Due To:

- Poison Ivy, Oak or Sumac
- Insect Bites
- Minor Skin Irritations

6 FL OZ (177 mL)